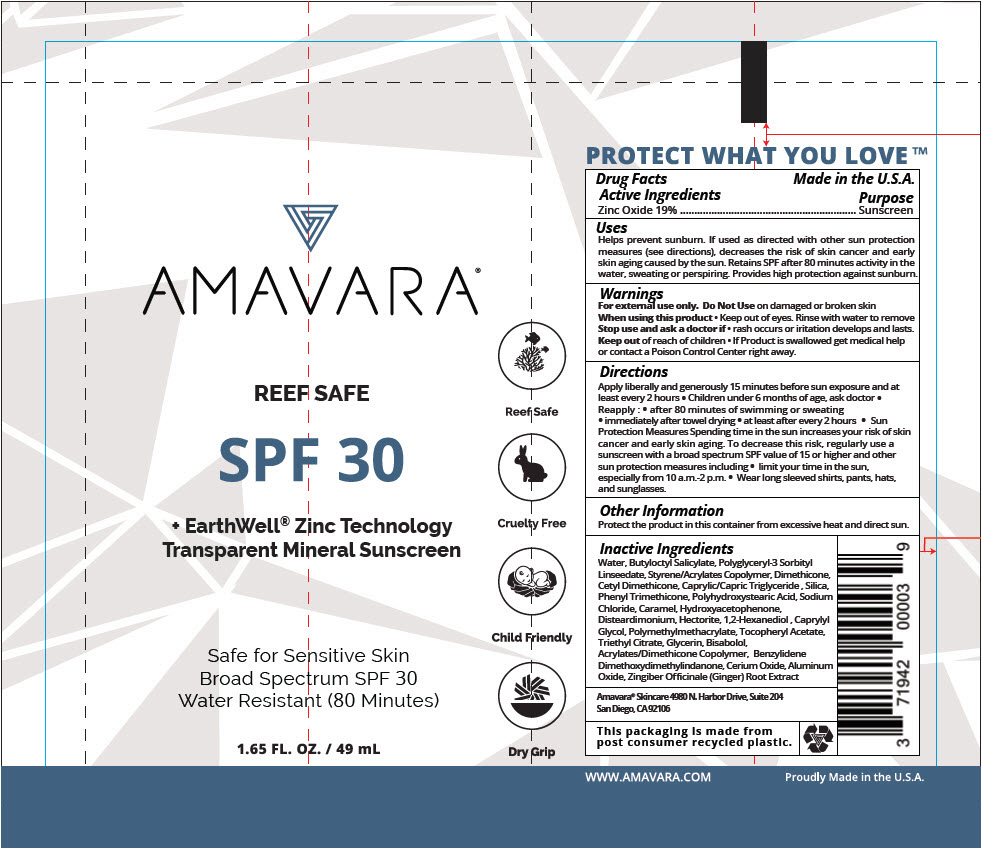 DRUG LABEL: AMAVARA TRANSPARENT MINERAL SUNSCREEN SPF30
NDC: 71942-101 | Form: LOTION
Manufacturer: Amavara, Inc
Category: otc | Type: HUMAN OTC DRUG LABEL
Date: 20190416

ACTIVE INGREDIENTS: ZINC OXIDE 190 mg/1 mL
INACTIVE INGREDIENTS: SODIUM CHLORIDE; CAPRYLYL GLYCOL; TRIETHYL CITRATE; BUTYLOCTYL SALICYLATE; ALUMINUM OXIDE; DISTEARDIMONIUM HECTORITE; POLY(METHYL METHACRYLATE; 450000 MW); GLYCERIN; GINGER; POLYHYDROXYSTEARIC ACID (2300 MW); BENZYLIDENE DIMETHOXYDIMETHYLINDANONE; CERIC OXIDE; PHENYL TRIMETHICONE; CARAMEL; 1,2-HEXANEDIOL; DIMETHICONE; MEDIUM-CHAIN TRIGLYCERIDES; SILICON DIOXIDE; HYDROXYACETOPHENONE; .ALPHA.-TOCOPHEROL ACETATE; LEVOMENOL; WATER; CETYL DIMETHICONE 25; STYRENE/ACRYLAMIDE COPOLYMER (500000 MW)

AMAVARA® TRANSPARENT MINERAL SUNSCREEN LOTION SPF30
EARTHWELL® ZINC TECHNOLOGY, REEF SAFE

Drug Facts

Active Ingredients

Zinc Oxide 19%

Purpose

Sunscreen

Uses

Helps prevent sunburn. If used as directed with other sun protection measures (see directions), decreases the risk of skin cancer and early skin aging caused by the sun. Retains SPF after 80 minutes activity in the water, sweating or perspiring. Provides high protection against sunburn.

Warnings

For external use only.

Do Not Use on damaged or broken skin

When using this product

- Keep out of eyes. Rinse with water to remove

Stop use and ask a doctor if

- rash occurs or iritation develops and lasts.

Keep out of reach of children

- If Product is swallowed get medical help or contact a Poison Control Center right away.

Directions

Apply liberally and generously 15 minutes before sun exposure and at least every 2 hours

- Children under 6 months of age, ask doctor
- Reapply :
  - after 80 minutes of swimming or sweating
  - immediately after towel drying
  - at least after every 2 hours
- Sun Protection Measures Spending time in the sun increases your risk of skin cancer and early skin aging. To decrease this risk, regularly use a sunscreen with a broad spectrum SPF value of 15 or higher and other sun protection measures including
  - limit your time in the sun, especially from 10 a.m.-2 p.m.
  - Wear long sleeved shirts, pants, hats, and sunglasses.

Other Information

Protect the product in this container from excessive heat and direct sun.

Inactive Ingredients

Water, Butyloctyl Salicylate, Polyglyceryl-3 Sorbityl Linseedate, Styrene/Acrylates Copolymer, Dimethicone, Cetyl Dimethicone, Caprylic/Capric Triglyceride , Silica, Phenyl Trimethicone, Polyhydroxystearic Acid, Sodium Chloride, Caramel, Hydroxyacetophenone, Disteardimonium, Hectorite, 1,2-Hexanediol , Caprylyl Glycol, Polymethylmethacrylate, Tocopheryl Acetate, Triethyl Citrate, Glycerin, Bisabolol, Acrylates/Dimethicone Copolymer, Benzylidene Dimethoxydimethylindanone, Cerium Oxide, Aluminum Oxide, Zingiber Officinale (Ginger) Root Extract

PRINCIPAL DISPLAY PANEL - 49 mL Tube Label

AMAVARA®

REEF SAFE

SPF 30

+ EarthWell® Zinc Technology
Transparent Mineral Sunscreen

Safe for Sensitive Skin
Broad Spectrum SPF 30
Water Resistant (80 Minutes)

1.65 FL. OZ. / 49 mL

Reef Safe

Cruelty Free

Child Friendly

Dry Grip